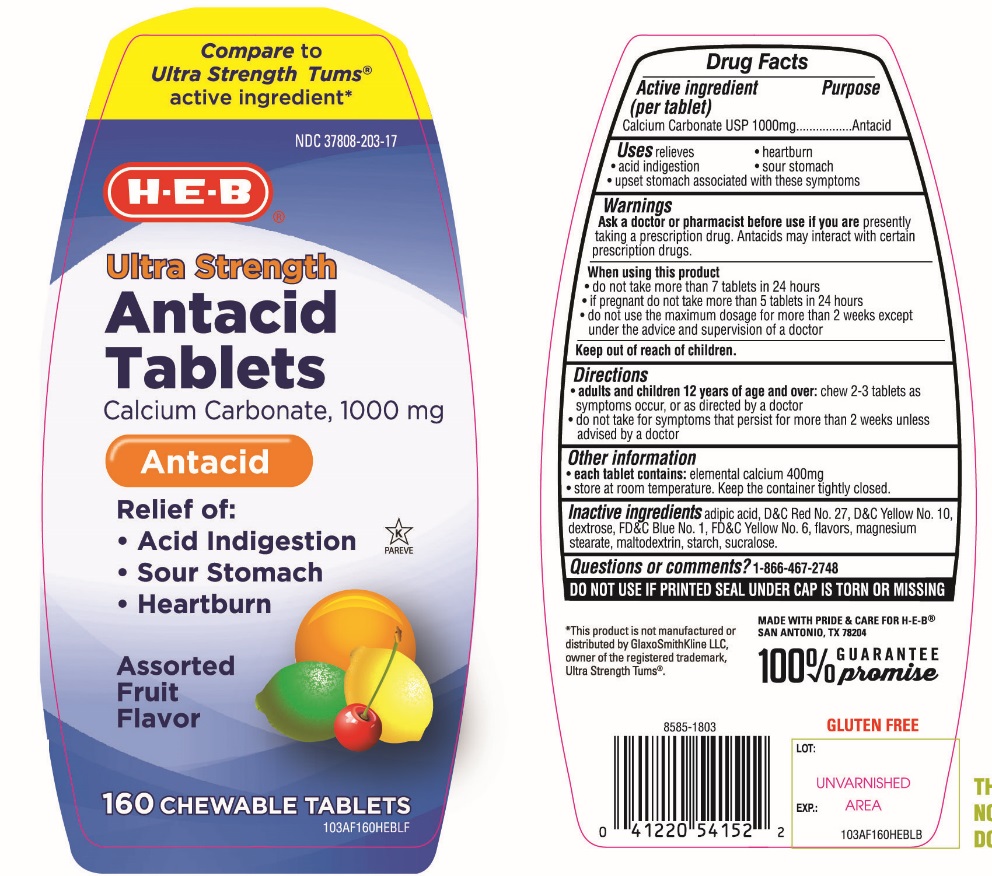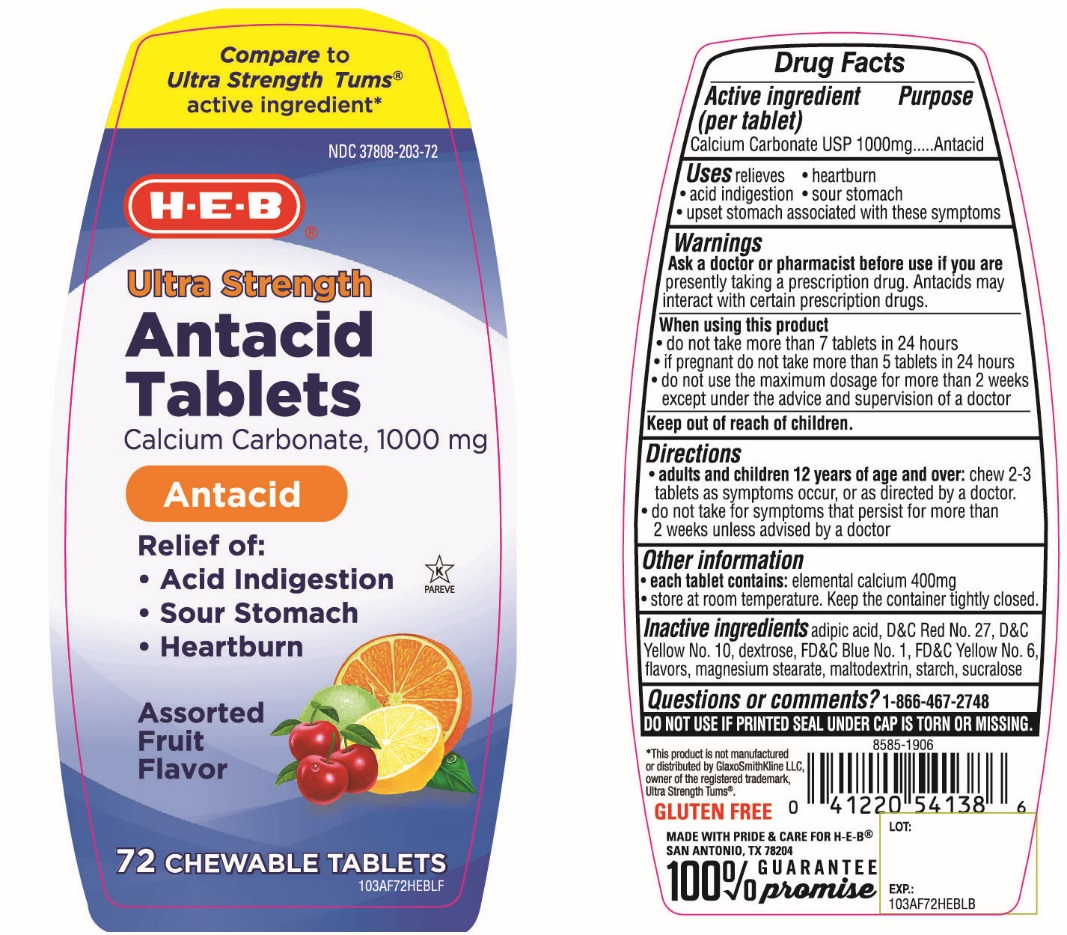 DRUG LABEL: HEB Ultra Strength

NDC: 37808-203 | Form: TABLET, CHEWABLE
Manufacturer: HEB
Category: otc | Type: HUMAN OTC DRUG LABEL
Date: 20251003

ACTIVE INGREDIENTS: CALCIUM CARBONATE 1000 mg/1 1
INACTIVE INGREDIENTS: ADIPIC ACID; D&C RED NO. 27; D&C YELLOW NO. 10; DEXTROSE, UNSPECIFIED FORM; FD&C BLUE NO. 1; FD&C YELLOW NO. 6; MAGNESIUM STEARATE; MALTODEXTRIN; STARCH, CORN; SUCRALOSE

HEB Ultra Strength Assorted fruits Flavor Chewable Tablets

Active ingredient (per tablet)

Calcium Carbonate USP 1,000 mg

Purpose

Antacid

Uses

relieves

• heartburn

• sour stomach

• acid indigestion

• upset stomach associated with these symptoms

Warnings

Ask a doctor or pharmacist before use if you are presentlytaking a prescription drug. Antacids may interact with certain prescription drugs.

When using this product

- do not take more than 7 tablets in 24 hours
- if pregnant do not take more than 5 tablets in 24 hours
- do not use the maximum dosage for more than 2 weeks except under the advice and supervision of a doctor.

Directions

- adults and children 12 years of age and over:chew 2-3 tablets as symptoms occur, or as directed by a doctor
- do not take for symptoms that persist for more than 2 weeks unless advised by a doctor

Other information

- each tablet contains : elemental calcium 400 mg
- store at room temperature. Keep the container tightly closed

Inactive ingredients

adipic acid, D&C Red No. 27, D&C Yellow No. 10, dextrose, FD&C Blue No. 1, FD&C Yellow No. 6, flavor, magnesium stearate, maltodextrin, starch, sucralose.

Questions or comments?

1-866-467-2748

SAFETY SEALED: DO NOT USE IF PRINTED SEAL UNDER CAP IS TORN OR MISSING

Package/Label Principal Display Panel

H-E-B®

Compare to Ultra Strength Tums®active ingredients*

Antacid Tablets 1000

ULTRA STRENGTH

Antacid Tablets

Calcium Carbonate 1000mg/ Antacid

Relieves of:

- Acid indigestion
- Sour Stomach
- Heartburn

Assorted Fruit Flavors

GLUTEN-FREE

100% GURANTEE promise

MADE WITH PRIDE & CARE FOR HEB®SAN ANTONIO, TX 78204

*This product is not manufactured and distributed by GlaxoSmithKline LLC, owner of the registered trademark, Ultra Strength Tums®

Package Label 160 Chewable Tablets